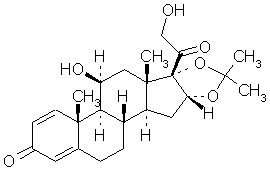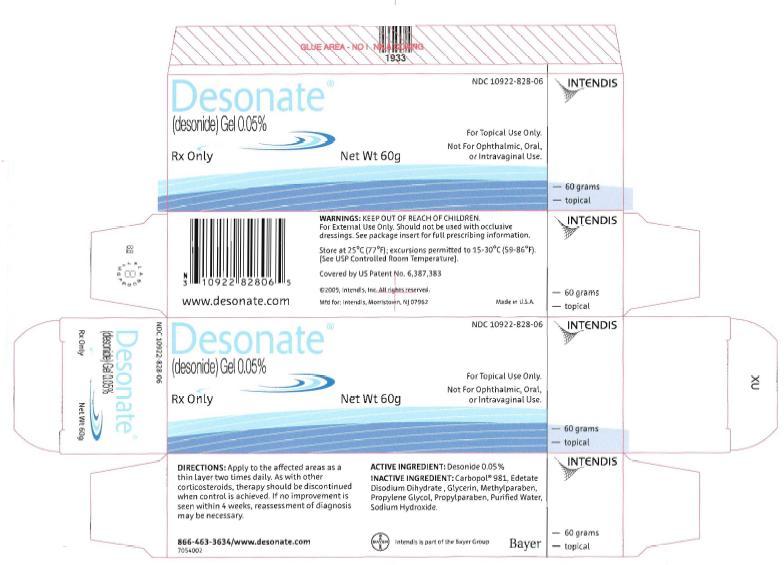 DRUG LABEL: DESONATE
NDC: 10922-828 | Form: GEL
Manufacturer: Intendis Inc.
Category: prescription | Type: HUMAN PRESCRIPTION DRUG LABEL
Date: 20101108

ACTIVE INGREDIENTS: DESONIDE 0.5 mg/1 g
INACTIVE INGREDIENTS: WATER; GLYCERIN; PROPYLENE GLYCOL; EDETATE DISODIUM; METHYLPARABEN; PROPYLPARABEN; SODIUM HYDROXIDE

HIGHLIGHTS OF PRESCRIBING INFORMATION

These highlights do not include all the information needed to use DESONATE Gel safely and effectively. See full prescribing information for DESONATE Gel.
DESONATE (desonide) Gel for topical use only
Initial U.S. Approval: 1972

1 INDICATIONS AND USAGE

Desonate® is a corticosteroid indicated for the topical treatment of mild to moderate atopic dermatitis in patients 3 months of age and older. (1)

2 DOSAGE AND ADMINISTRATION

- Apply as a thin layer to the affected areas two times daily and rub in gently. (2)
- Therapy should be discontinued when control is achieved. (2)
- If no improvement is seen within 4 weeks, reassessment of diagnosis may be necessary. (2)
- Should not be used with occlusive dressings. (2)
- Treatment beyond 4 consecutive weeks is not recommended. (2)

For topical use only. Not for oral, ophthalmic, or intravaginal use. (2)

3 DOSAGE FORMS AND STRENGTHS

Gel, 0.05%; (0.5mg/g) desonide in a translucent to opaque gel

4 CONTRAINDICATIONS

History of hypersensitivity to any of the components of the preparation.

5 WARNINGS AND PRECAUTIONS

- Topical corticosteroids can produce reversible hypothalamic pituitary adrenal (HPA) axis suppression, Cushing's syndrome and unmask latent diabetes. (5.1)
- Systemic absorption may require evaluation for HPA axis suppression (5.1).
- Modify use should HPA axis suppression develop (5.1)
- Potent corticosteroids, use on large areas, prolonged use or occlusive use may increase systemic absorption (5.1)
- Local adverse reactions may include atrophy, striae, irritation, acneiform eruptions, hypopigmentation, and allergic contact dermatitis and may be more likely with occlusive use or more potent corticosteroids. (5.2, 5.4, 6)
- Children may be more susceptible to systemic toxicity when treated with topical corticosteroids. (5.1, 8.4)

6 ADVERSE REACTIONS

The most common adverse reactions (incidence ≥ 1%) are headache and application site burning. (6)

To report SUSPECTED ADVERSE REACTIONS, contact Intendis, Inc. at 1-866-463-3634 or FDA at 1-800-FDA-1088 or www.fda.gov/medwatch

8 USE IN SPECIFIC POPULATIONS

Safety and effectiveness of Desonate in pediatric patients less than 3 months of age have not been evaluated, and therefore its use in this age group is not recommended. (8.4)

FULL PRESCRIBING INFORMATION

1 INDICATIONS AND USAGE

Desonate is indicated for the treatment of mild to moderate atopic dermatitis in patients 3 months of age and older.

Patients should be instructed to use Desonate for the minimum amount of time as necessary to achieve the desired results because of the potential for Desonate to suppress the hypothalamic-pituitary-adrenal (HPA) axis [see Warnings and Precautions (5.1)]. Treatment should not exceed 4 consecutive weeks [see Dosage and Administration (2)].

2 DOSAGE AND ADMINISTRATION

Apply a thin layer to the affected areas two times daily and rub in gently. Discontinue use when control is achieved. If no improvement is seen within 4 weeks, reassessment of diagnosis may be necessary. Treatment beyond 4 consecutive weeks is not recommended. Do not use with occlusive dressings. Avoid contact with eyes or other mucous membranes.

For topical use only. Not for oral, ophthalmic, or intravaginal use.

3 DOSAGE FORMS AND STRENGTHS

Gel, 0.05%; (0.5mg/g) desonide in a translucent to opaque gel

4 CONTRAINDICATIONS

Desonate is contraindicated in those patients with a history of hypersensitivity to any of the components of the preparation.

5 WARNINGS AND PRECAUTIONS

5.1 Effects on Endocrine System

Systemic absorption of topical corticosteroids can produce reversible hypothalamic-pituitary-adrenal (HPA) axis suppression with the potential for clinical glucocorticosteroid insufficiency. This may occur during treatment or upon withdrawal of the topical corticosteroid.

The effect of Desonate on HPA axis function was investigated in pediatric subjects, 6 months to 6 years old, with atopic dermatitis covering at least 35% of their body, who were treated with Desonate twice daily for 4 weeks. One of 37 subjects (3%) displayed adrenal suppression after 4 weeks of use, based on the cosyntropin stimulation test. As follow-up evaluation of the subject's adrenal axis was not performed, it is unknown whether the suppression was reversible [see Use In Specific Populations (8.4) and Clinical Pharmacology (12.2)].

Pediatric patients may be more susceptible than adults to systemic toxicity from equivalent doses of Desonate due to their larger skin surface-to-body mass ratios [see Use In Specific Populations (8.4)].

Because of the potential for systemic absorption, use of topical corticosteroids may require that patients be periodically evaluated for HPA axis suppression. Factors that predispose a patient using a topical corticosteroid to HPA axis suppression include the use of more potent steroids, use over large surface areas, use over prolonged periods, use under occlusion, use on an altered skin barrier, and use in patients with liver failure.

An ACTH stimulation test may be helpful in evaluating patients for HPA axis suppression. If HPA axis suppression is documented, an attempt should be made to gradually withdraw the drug, to reduce the frequency of application, or to substitute a less potent steroid. Manifestations of adrenal insufficiency may require supplemental systemic corticosteroids. Recovery of HPA axis function is generally prompt and complete upon discontinuation of topical corticosteroids.

Cushing’s syndrome, hyperglycemia, and unmasking of latent diabetes mellitus can also result from systemic absorption of topical corticosteroids.

Use of more than one corticosteroid-containing product at the same time may increase the total systemic corticosteroid exposure.

5.2 Local Adverse Reactions with Topical Corticosteroids

Local adverse reactions may be more likely to occur with occlusive use, prolonged use or use of higher potency corticosteroids. Reactions may include skin atrophy, striae, telangiectasias, burning, itching, irritation, dryness, folliculitis, acneiform eruptions, hypopigmentation, perioral dermatitis, allergic contact dermatitis, secondary infection, and miliaria. Some local adverse reactions may be irreversible.

5.3 Concomitant Skin Infections

If concomitant skin infections are present or develop during treatment, an appropriate antifungal or antibacterial agent should be used. If a favorable response does not occur promptly, use of Desonate should be discontinued until the infection is adequately controlled.

5.4 Skin Irritation

If irritation develops, Desonate should be discontinued and appropriate therapy instituted. Allergic contact dermatitis with corticosteroids is usually diagnosed by observing failure to heal rather than noting a clinical exacerbation as with most topical products not containing corticosteroids. Such an observation should be corroborated with appropriate diagnostic patch testing.

6 ADVERSE REACTIONS

Because clinical trials are conducted under widely varying conditions, adverse reaction rates observed in the clinical trials of a drug cannot be directly compared to rates in the clinical trials of another drug and may not reflect the rates observed in practice.

In controlled clinical studies of 425 Desonate treated subjects and 157 Vehicle-treated subjects, adverse events occurred at the application site in 3% of subjects treated with Desonate and the incidence rate was not higher compared with vehicle-treated subjects. The most common local adverse events in Desonate treated subjects were application site burning in 1% (4/425) and rash in 1% (3/425) followed by application site pruritus in <1% (2/425).

Adverse events that resulted in premature discontinuation of study drug in Desonate treated subjects were telangiectasia and worsening of atopic dermatitis in one subject each. Additional adverse events observed during clinical trials for patients treated with Desonate included headache in 2% (8/425) compared with 1% (2/157) in those treated with vehicle.

The following additional local adverse reactions have been reported infrequently with topical corticosteroids. They may occur more frequently with the use of occlusive dressings, especially with higher potency corticosteroids. These reactions are listed in an approximate decreasing order of occurrence: folliculitis, acneiform eruptions, hypopigmentation, perioral dermatitis, secondary infection, skin atrophy, striae, and miliaria.

8 USE IN SPECIFIC POPULATIONS

8.1 Pregnancy

Teratogenic effects: Pregnancy Category C:

There are no adequate and well-controlled studies in pregnant women. Therefore, Desonate should be used during pregnancy only if the potential benefit justifies the potential risk to the fetus.

Corticosteroids have been shown to be teratogenic in laboratory animals when administered systemically at relatively low dosage levels. Some corticosteroids have been shown to be teratogenic after dermal application in laboratory animals.

No reproductive studies in animals have been performed with Desonate. Dermal embryofetal development studies were conducted in rats and rabbits with a desonide cream, 0.05% formulation. Topical doses of 0.2, 0.6, and 2.0 g cream/kg/day of a desonide cream, 0.05% formulation or 2.0 g/kg of the cream base were administered topically to pregnant rats (gestational days 6-15) and pregnant rabbits (gestational days 6-18). Maternal body weight loss was noted at all dose levels of the desonide cream, 0.05% formulation in rats and rabbits. Teratogenic effects characteristic of corticosteroids were noted in both species. The desonide cream, 0.05% formulation was teratogenic in rats at topical doses of 0.6 and 2.0 g cream/kg/day and in rabbits at a topical dose of 2.0 g cream/kg/day. No teratogenic effects were noted for the desonide cream, 0.05% formulation at a topical dose of 0.2 g cream/kg/day in rats and 0.6 g cream/kg/day in rabbits. These doses (0.2 g cream/kg/day and 0.6 g cream/kg/day) are similar to the maximum recommended human dose based on body surface area comparisons.

8.3 Nursing Mothers

Systemically administered corticosteroids appear in human milk and could suppress growth, interfere with endogenous corticosteroid production, or cause other untoward effects. It is not known whether topical administration of corticosteroids could result in sufficient systemic absorption to produce detectable quantities in human milk. Because many drugs are excreted in human milk, caution should be exercised when Desonate is administered to a nursing woman.

8.4 Pediatric Use

Safety and effectiveness of Desonate in pediatric patients less than 3 months of age have not been evaluated, and therefore its use in this age group is not recommended.

The effect of Desonate on HPA axis function was investigated in pediatric subjects, with atopic dermatitis covering at least 35% of their body, who were treated with Desonate twice daily for 4 weeks. One of 37 subjects (3%) displayed adrenal suppression after 4 weeks of use, based on the cosyntropin stimulation test [see Warnings and Precautions (5.1)].

In controlled clinical studies in subjects 3 months to 18 years of age, 425 subjects were treated with Desonate and 157 subjects were treated with vehicle [see Adverse Reactions (6) and Clinical Studies (14)].

Because of a higher ratio of skin surface area to body mass, pediatric patients are at a greater risk than adults of HPA axis suppression when they are treated with topical corticosteroids. They are therefore also at greater risk of glucocorticosteroid insufficiency after withdrawal of treatment and of Cushing's syndrome while on treatment.

Adverse effects, including striae, have been reported with inappropriate use of topical corticosteroids in infants and children. HPA axis suppression, Cushing's syndrome, linear growth retardation, delayed weight gain and intracranial hypertension have been reported in children receiving topical corticosteroids. Manifestations of adrenal suppression in children include low plasma cortisol levels and absence of response to ACTH stimulation. Manifestations of intracranial hypertension include bulging fontanelles, headaches, and bilateral papilledema.

8.5 Geriatric Use

Clinical studies of Desonate did not include patients aged 65 and older to determine if they respond differently than younger patients. Treatment of this patient population should reflect the greater frequency of decreased hepatic, renal, or cardiac function, and of concomitant disease or other drug therapy.

10 OVERDOSAGE

Topically applied Desonate can be absorbed in sufficient amounts to produce systemic effects [see Warnings and Precautions (5.1)].

11 DESCRIPTION

Desonate contains desonide [(pregna-1, 4-diene-3, 20-dione,11, 21-dihydroxy-16, 17-[(1-methylethylidene) bis(oxy)]-,(11β,16α)]- a synthetic nonfluorinated corticosteroid for topical dermatologic use. Chemically, desonide is C24H32O6. It has the following structural formula:

Desonide has the molecular weight of 416.52. It is a white to off-white odorless powder which is soluble in methanol and practically insoluble in water. Each gram of Desonate contains 0.5 mg of desonide in an aqueous gel base of purified water, glycerin, propylene glycol, edetate disodium dihydrate, methylparaben, propylparaben, sodium hydroxide, and Carbopol® 981.

12 CLINICAL PHARMACOLOGY

12.1 Mechanism of Action

The mechanism of action of desonide is unknown.

12.2 Pharmacodynamics

In an HPA axis suppression study, one of 37 (3%) pediatric subjects, 6 months to 6 years old, with moderate to severe atopic dermatitis covering at least 35% body surface area who applied Desonate experienced suppression of the adrenal glands following 4 weeks of therapy [see Warnings And Precautions (5.1) and Use In Specific Populations (8.4)]. A follow-up evaluation of the subject's adrenal axis was not performed; it is unknown whether the suppression was reversible.

12.3 Pharmacokinetics

The extent of percutaneous absorption of topical corticosteroids is determined by many factors, including product formulation and the integrity of the epidermal barrier. Occlusion, inflammation and/or other disease processes in the skin may also increase percutaneous absorption. Once absorbed through the skin, topical corticosteroids are handled through pharmacokinetic pathways similar to systemically administered corticosteroids. They are metabolized primarily in the liver and then are excreted by the kidneys. Some corticosteroids and their metabolites are also excreted in the bile.

13 NONCLINICAL TOXICOLOGY

13.1 Carcinogenesis, Mutagenesis, Impairment of Fertility

Long-term animal studies have not been performed to evaluate the carcinogenic or photoco-carcinogenic potential of Desonate or the effect of desonide on fertility. Desonide revealed no evidence of mutagenic potential based on the results of an in vitro genotoxicity test (Ames assay) and an in vivo genotoxicity test (mouse micronucleus assay). Desonide was positive without S9 activation and was equivocal with S9 activation in an in vitro mammalian cell mutagenesis assay (L5178YITK+ mouse lymphoma assay). A dose response trend was not noted in this assay.

14 CLINICAL STUDIES

In two randomized vehicle-controlled clinical studies, subjects 3 months to 18 years of age with mild to moderate atopic dermatitis were treated twice daily for 4 weeks with either Desonate or vehicle. Treatment success was defined as achieving clear or almost clear on the Investigator's Global Severity Score (IGSS) with at least a 2-point change (decrease) from the subject's baseline IGSS when compared to the Week 4 IGSS. The results of the 2 clinical trials are summarized in Table 1:

Table 1: Subjects Achieving Treatment Success
Clinical Trial 1
Desonate; N = 289 | Vehicle; N = 92
128 (44%) | 13 (14%)
Clinical Trial 2
Desonate; N = 136 | Vehicle; N = 65
38 (28%) | 4 (6%)

16 HOW SUPPLIED/STORAGE AND HANDLING

Desonate is a translucent to opaque gel supplied in 60g tubes in cartons containing 1x 60g tube (NDC 10922-828-06), or a 2 x 60g tube Twin Pack (NDC 10922-828-12).

Storage:

Store at 25°C (77°F); excursions permitted to15-30°C (59-86°F). [See USP Controlled Room Temperature].

Keep out of reach of children.

17 PATIENT COUNSELING INFORMATION

Patients using topical corticosteroids should receive the following information and instructions:

- This medication is to be used as directed by the physician. It is for external use only. Avoid contact with the eyes.
- This medication should not be used for any disorder other than that for which it was prescribed.
- Unless directed by the physician, the treated skin area should not be bandaged or otherwise covered or wrapped so as to be occlusive.
- Unless directed by a physician, this medication should not be used on the underarm or groin areas of pediatric patients.
- Parents of pediatric patients should be advised not to use Desonate in the treatment of diaper dermatitis. Desonate should not be applied in the diaper area, as diapers or plastic pants may constitute occlusive dressing [see Dosage and Administration (2)].
- Patients should report to their physician any signs of local adverse reactions.
- Other corticosteroid-containing products should not be used with Desonate without first consulting with the physician.
- As with other corticosteroids, therapy should be discontinued when control is achieved. If no improvement is seen within 4 weeks, contact the physician.

© 2010, Intendis, Inc. All rights reserved. June 2010

Manufactured by Contract Pharmaceuticals Limited, Buffalo, NY 14213

Distributed by:
Intendis
Morristown, NJ 07962

Intendis is part of the Bayer Group

6706903

The Desonate logo is a registered trademark of Intendis, Inc.
Covered by US Patent No. 6,387,383

The following is a representative example of Desonate labeling. See the "How Supplied" section for a complete listing of all components.

PACKAGE LABEL

Desonate 60 g Carton

NDC 10922-828-06

Desonate®

(desonide) Gel 0.05%

Rx Only Net Wt 60 g

For Topical Use Only. Not for Ophthalmic, Oral, or Intravaginal Use.

INTENDIS